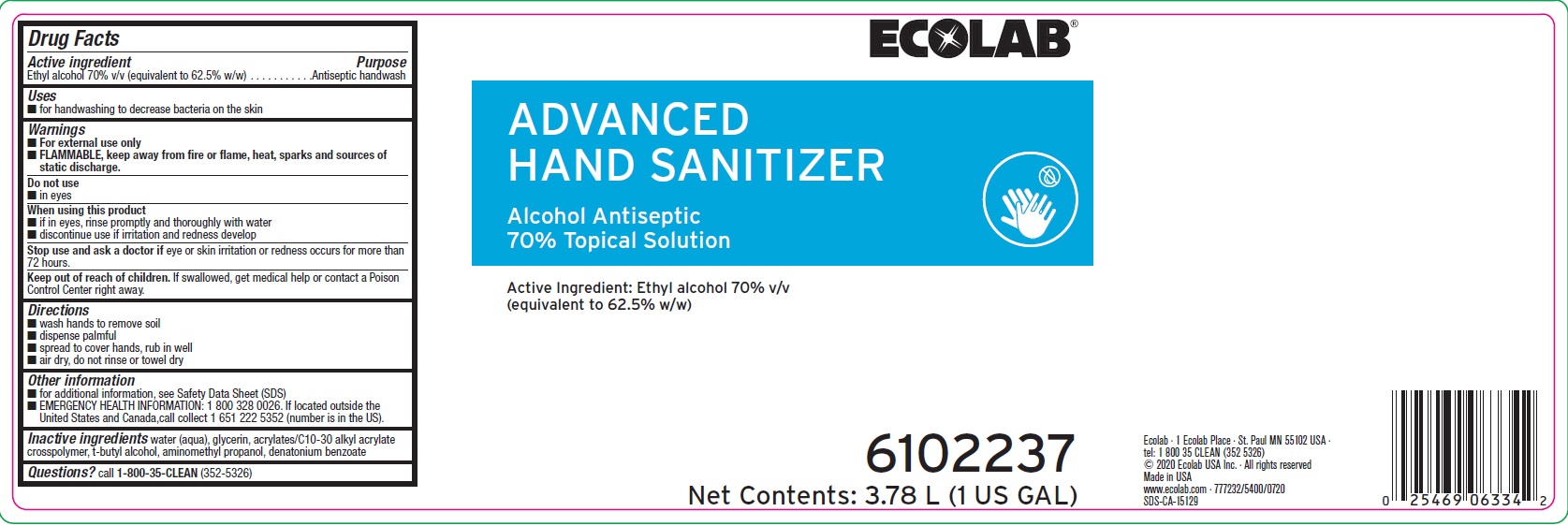 DRUG LABEL: Ecolab Advanced Hand Sanitizer
NDC: 47593-636 | Form: SOLUTION
Manufacturer: Ecolab Inc.
Category: otc | Type: HUMAN OTC DRUG LABEL
Date: 20251103

ACTIVE INGREDIENTS: ALCOHOL 70 mL/100 mL
INACTIVE INGREDIENTS: WATER; GLYCERIN; CARBOMER INTERPOLYMER TYPE A (ALLYL SUCROSE CROSSLINKED); TERT-BUTYL ALCOHOL; AMINOMETHYLPROPANOL; DENATONIUM BENZOATE

Drug Facts

Active ingredient

Ethyl alcohol 70% v/v (equivalent to 62.5% w/w)

Purpose

Antiseptic handwash

Uses

- For handwashing to decrease bacteria on the skin

Warnings

- For external use only.
- Flammable, keep away from fire or flame, heat, sparks and sources of static discharge

Do not use

- In eyes

When using this product

- If in eyes, rinse promptly and thoroughly with water
- Discontinue use if irritation and redness develop

Stop use and ask a doctor if

- Skin irritation or redness occurs for more than 72 hours

Keep out of reach of children. If swallowed, get medical help or contact a Poison Control Center right away.

Directions

- wash hands to remove soil
- dispense palmful
- spread to cover hands, rub in well
- air dry, do not rinse or towel dry

Other information

- for additional information, see Safety Data Sheet (SDS)
- EMERGENCY HEALTH INFORMATION: 1 800 328 0026. If located outside the United States and Canada, call collect 1 651 222 5352 (number is in the US).

INACTIVE INGREDIENT

Inactive ingredients water (aqua), glycerin, acrylates/C10-30 alkyl acrylate crosspolymer, t-butyl alcohol, aminomethyl propanol, denatonium benzoate

Questions? call 1-800-35-CLEAN (352-5326)

Representative label and principal display panel

ECOLAB

ADVANCED

HAND SANITIZER

Alcohol Antiseptic

70% Topical Solution

Active Ingredient: Ethyl alcohol 70% v/v (equivalent to 62.5% w/w)

6102237

Net Contents: 3.78 L (1 US GAL)

Ecolab · 1 Ecolab Place · St. Paul MN 55102 USA ·

tel: 1 800 35 CLEAN (352 5326)

© 2020 Ecolab USA Inc. · All rights reserved

Made in USA

www.ecolab.com · 777232/5400/0720

SDS-CA-15195